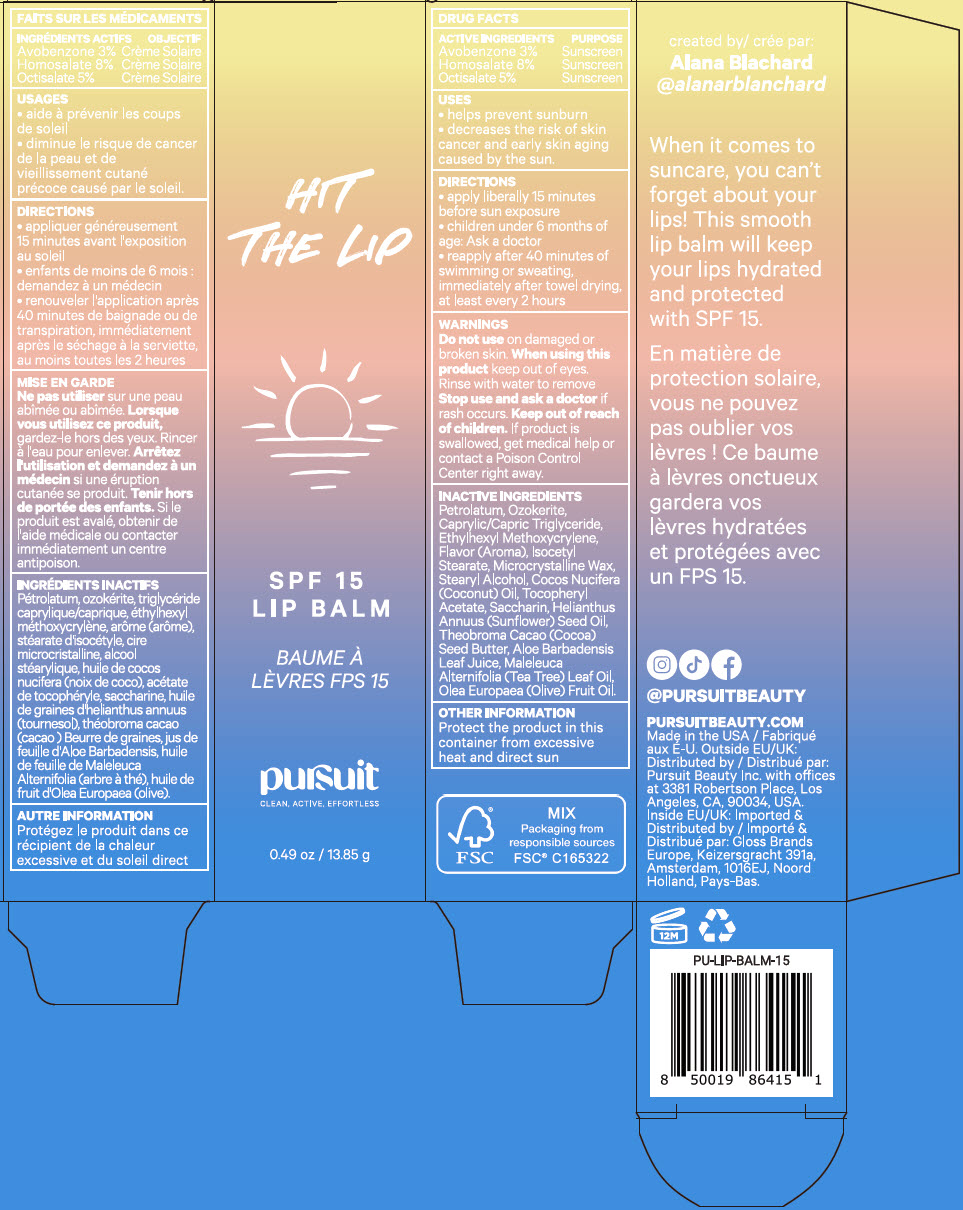 DRUG LABEL: Pursuit Hit the Lip SPF 15 Lip Balm
NDC: 83040-002 | Form: LIPSTICK
Manufacturer: Pursuit Beauty Inc.
Category: otc | Type: HUMAN OTC DRUG LABEL
Date: 20221128

ACTIVE INGREDIENTS: AVOBENZONE 3 g/100 g; HOMOSALATE 8 g/100 g; OCTISALATE 5 g/100 g
INACTIVE INGREDIENTS: PETROLATUM 38.8 g/100 g; CERESIN 16.5 g/100 g; MEDIUM-CHAIN TRIGLYCERIDES 12 g/100 g; ETHYLHEXYL METHOXYCRYLENE 8 g/100 g; ISOCETYL STEARATE 2.3 g/100 g; MICROCRYSTALLINE WAX 1.1 g/100 g; STEARYL ALCOHOL 0.7 g/100 g; COCONUT OIL 0.5 g/100 g; .ALPHA.-TOCOPHEROL ACETATE, DL- 0.5 g/100 g; SACCHARIN 0.2 g/100 g; SUNFLOWER OIL 0.18 g/100 g; COCOA BUTTER 0.1 g/100 g; ALOE VERA LEAF 0.1 g/100 g; TEA TREE OIL 0.01 g/100 g; OLIVE OIL 0.01 g/100 g

Pursuit Hit the Lip SPF 15 Lip Balm

Drug Facts

ACTIVE INGREDIENT

Active Ingredients | Purpose
Avobenzone 3.0% | Sunscreen
Homosalate 8.0% | Sunscreen
Octisalate 5.0% | Sunscreen

Uses

- helps prevent sunburn
- decreases the risk of skin cancer and early skin aging caused by the sun.

Warnings

Do not use on damaged or broken skin

When using this product keep out of eyes. Rinse with water to remove

Stop use and ask a doctor if rash occurs

Keep out of reach of children. If product is swallowed, get medical help or contact a Poison Control Center right away.

Directions

- apply liberally 15 minutes before sun exposure
- children under 6 months of age: Ask a doctor
- reapply after 40 minutes of swimming or sweating, immediately after towel drying, at least every 2 hours

Inactive Ingredients

Petrolatum, Ozokerite, Caprylic/Capric Triglyceride, Ethylhexyl Methoxycrylene, Flavor (Aroma), Isocetyl Stearate, Microcrystalline Wax, Stearyl Alcohol, Cocos Nucifera (Coconut) Oil, Tocopheryl Acetate, Saccharin, Helianthus Annuus (Sunflower) Seed Oil, Theobroma Cacao (Cocoa) Seed Butter, Aloe Barbadensis Leaf Juice, Maleleuca Alternifolia (Tea Tree) Leaf Oil, Olea Europaea (Olive) Fruit Oil.

Other Information

Protect the product in this container from excessive heat and direct sun

Distributed by:
Pursuit Beauty Inc. with offices
at 3381 Robertson Place, Los
Angeles, CA, 90034, USA.

Imported &
Distributed by:
Gloss Brands
Europe, Keizersgracht 391a,
Amsterdam, 1016EJ, Noord
Holland, Pays-Bas.

PRINCIPAL DISPLAY PANEL - 13.85 g Cylinder Carton

HIT
THE LIP

SPF 15
LIP BALM

pursuit
CLEAN, ACTIVE, EFFORTLESS

0.49 oz / 13.85 g